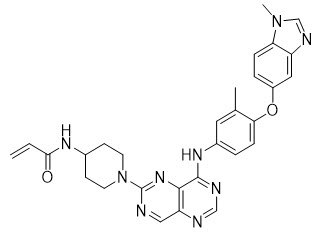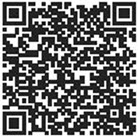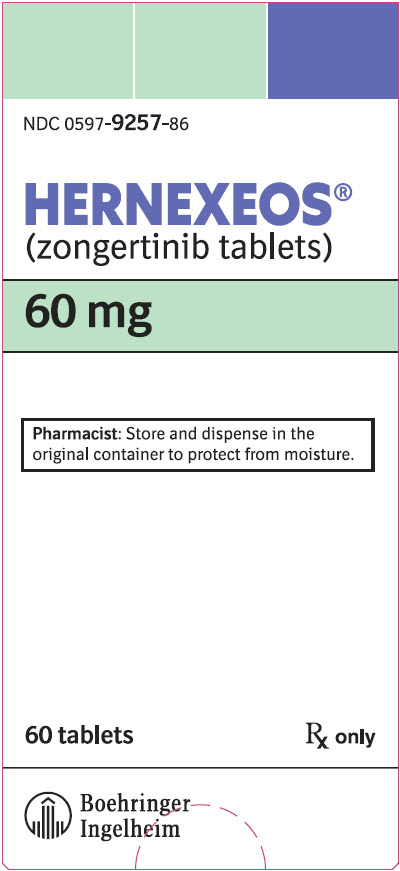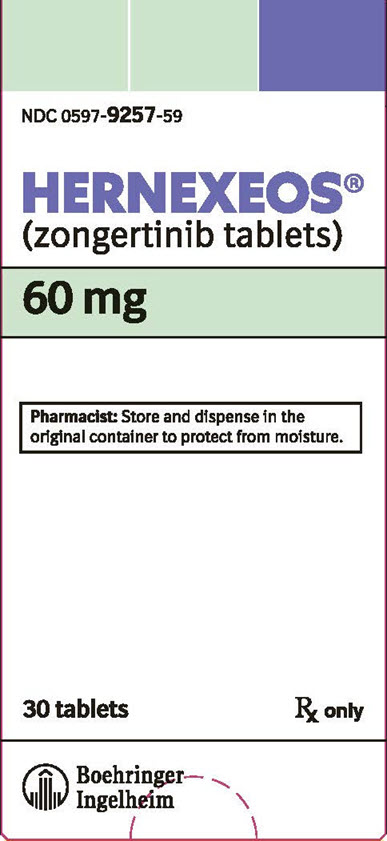 DRUG LABEL: HERNEXEOS
NDC: 0597-9257 | Form: TABLET, FILM COATED
Manufacturer: Boehringer Ingelheim Pharmaceuticals, Inc.
Category: prescription | Type: HUMAN PRESCRIPTION DRUG LABEL
Date: 20260106

ACTIVE INGREDIENTS: ZONGERTINIB 60 mg/1 1

HIGHLIGHTS OF PRESCRIBING INFORMATION

These highlights do not include all the information needed to use HERNEXEOS safely and effectively. See full prescribing information for HERNEXEOS.
HERNEXEOS® (zongertinib tablets), for oral use
Initial U.S. Approval: 2025

1 INDICATIONS AND USAGE

HERNEXEOS is a kinase inhibitor indicated for the treatment of adult patients with unresectable or metastatic non-squamous non-small cell lung cancer (NSCLC) whose tumors have HER2 (ERBB2) tyrosine kinase domain activating mutations, as detected by an FDA-approved test, and who have received prior systemic therapy. (1)

This indication is approved under accelerated approval based on objective response rate and duration of response. Continued approval for this indication may be contingent upon verification and description of clinical benefit in a confirmatory trial. (1)

2 DOSAGE AND ADMINISTRATION

- Select patients for treatment with HERNEXEOS based on the presence of HER2 (ERBB2) tyrosine kinase domain activating mutations. (2.1)
- The recommended dosage of HERNEXEOS is based on body weight: (2.2)
  - < 90 kg: 120 mg (2.2)
  - ≥ 90 kg: 180 mg (2.2)
- Take HERNEXEOS orally once daily with or without food until disease progression or unacceptable toxicity. (2.2)

3 DOSAGE FORMS AND STRENGTHS

Tablets: 60 mg (3)

4 CONTRAINDICATIONS

None. (4)

5 WARNINGS AND PRECAUTIONS

- Hepatotoxicity: Monitor liver function tests including ALT, AST, and total bilirubin at baseline prior to administration, every 2 weeks during the first 12 weeks, and then monthly thereafter as clinically indicated, with more frequent testing in patients who develop transaminase elevations. Interrupt, reduce the dose, or permanently discontinue HERNEXEOS based on severity. (5.1)
- Left Ventricular Dysfunction: Before initiating, evaluate LVEF and monitor at regular intervals during treatment and as clinically indicated. Interrupt, reduce the dose, or permanently discontinue HERNEXEOS based on severity. (5.2)
- Interstitial Lung Disease/Pneumonitis: Monitor for new or worsening symptoms indicative of ILD/pneumonitis (e.g., dyspnea, cough, fever). Interrupt, reduce the dose, or permanently discontinue HERNEXEOS based on severity. (5.3)
- Embryo-Fetal Toxicity: Can cause fetal harm. Advise patients of the potential risk to a fetus and to use effective contraception. (5.4)

6 ADVERSE REACTIONS

Most common adverse reactions (≥ 20%) are diarrhea, hepatotoxicity, rash, fatigue, and nausea. (6.1)

The most common (≥ 2%) Grade 3 or 4 laboratory abnormalities were decreased lymphocytes, increased alanine aminotransferase, increased aspartate aminotransferase, decreased potassium, and increased gamma glutamyl transferase. (6.1)

To report SUSPECTED ADVERSE REACTIONS, contact Boehringer Ingelheim Pharmaceuticals, Inc. at 1-800-542-6257 or FDA at 1-800-FDA-1088 or www.fda.gov/medwatch.

7 DRUG INTERACTIONS

- Strong CYP3A Inducers: Avoid concomitant use with strong CYP3A inducers. If concomitant use cannot be avoided, increase HERNEXEOS dose. (7.1)
- BCRP Substrates: Avoid concomitant use with certain BCRP substrates where minimal concentration increase may lead to serious adverse reactions and consider alternative therapies. If concomitant use cannot be avoided, monitor patients closely for adverse reactions and follow recommendations provided in the BCRP substrate approved product labeling. For other BCRP substrates, monitor for increased adverse reactions and adjust the dosages of those substrates as clinically appropriate. (7.2)

8 USE IN SPECIFIC POPULATIONS

- Lactation: Advise not to breastfeed. (8.2)

FULL PRESCRIBING INFORMATION

1 INDICATIONS AND USAGE

HERNEXEOS is indicated for the treatment of adult patients with unresectable or metastatic non-squamous non-small cell lung cancer (NSCLC) whose tumors have HER2 (ERBB2) tyrosine kinase domain activating mutations, as detected by an FDA-approved test, and who have received prior systemic therapy [see Dosage and Administration (2.1)].

This indication is approved under accelerated approval based on objective response rate and duration of response [see Clinical Studies (14)]. Continued approval for this indication may be contingent upon verification and description of clinical benefit in a confirmatory trial.

2 DOSAGE AND ADMINISTRATION

2.1 Patient Selection

Select patients for treatment of unresectable or metastatic NSCLC based on the presence of HER2 (ERBB2) tyrosine kinase domain activating mutations in tumor specimens [see Clinical Studies (14)]. Information on FDA-approved tests for HER2 (ERBB2) tyrosine kinase domain activating mutations is available at: http://www.fda.gov/CompanionDiagnostics.

2.2 Recommended Dosage and Administration

The recommended dosage of HERNEXEOS is based on body weight:

- < 90 kg: 120 mg
- ≥ 90 kg: 180 mg

Take HERNEXEOS orally once daily with or without food until disease progression or unacceptable toxicity. Swallow HERNEXEOS tablets whole with water. Do not split, crush, or chew tablets.

Missed Dose

If a dose is missed within 12 hours, take the dose. If a dose is missed by more than 12 hours, skip the missed dose and take the next scheduled dose.

Vomited Dose

If a dose is vomited, do not take an additional dose. Take the next dose at the regularly scheduled time.

2.3 Dosage Modifications for Adverse Reactions

The recommended dose reductions for adverse reactions are presented in Table 1.

Table 1 Recommended HERNEXEOS Dose Reductions for Adverse Reactions
Current HERNEXEOS Dose | First Reduction | Second Reduction
180 mg | 120 mg | 60 mg
120 mg | 60 mg | Permanently discontinue
Permanently discontinue HERNEXEOS in patients who are unable to tolerate 60 mg once daily.

The recommended dosage modifications for adverse reactions are presented in Table 2.

Table 2 Recommended HERNEXEOS Dosage Modifications for Adverse Reactions
Adverse Reaction | Severity | Dosage Modification
Hepatotoxicity [see Warnings and Precautions (5.1)] | Grade 3 or 4 ALT and/or AST without increased total bilirubin | - Interrupt HERNEXEOS until recovered to ≤ Grade 1 or baseline. - Resume HERNEXEOS at reduced dose level.
Hepatotoxicity [see Warnings and Precautions (5.1)] | Grade 3 total bilirubin | - Interrupt HERNEXEOS until recovered to ≤ Grade 1 or baseline. - Resume HERNEXEOS at reduced dose level.
Hepatotoxicity [see Warnings and Precautions (5.1)] | Grade 4 total bilirubin | - Permanently discontinue HERNEXEOS.
Hepatotoxicity [see Warnings and Precautions (5.1)] | ALT or AST ≥ 3× ULN with total bilirubin ≥ 2× ULN | - Permanently discontinue HERNEXEOS.
Left Ventricular Dysfunction [see Warnings and Precautions (5.2)] | LVEF 40 to 50% and decrease from baseline of 10 to 19% | - Interrupt HERNEXEOS until recovered to ≤ Grade 1 or within 10% from baseline. - If recovered to ≤ Grade 1 in ≤ 4 weeks, resume HERNEXEOS at the same dose level. - If not recovered to ≤ Grade 1 within 4 weeks, permanently discontinue HERNEXEOS.
Left Ventricular Dysfunction [see Warnings and Precautions (5.2)] | LVEF 20 to 39% or ≥ 20% decrease from baseline | - Interrupt HERNEXEOS until recovered to ≤ Grade 1 or within 10% from baseline. - If recovered to ≤ Grade 1 in ≤ 4 weeks, resume HERNEXEOS at the reduced dose level. - If not recovered to ≤ Grade 1 within 4 weeks, permanently discontinue HERNEXEOS.
Left Ventricular Dysfunction [see Warnings and Precautions (5.2)] | Symptomatic Congestive Heart Failure | - Permanently discontinue HERNEXEOS.
Interstitial Lung Disease/Pneumonitis [see Warnings and Precautions (5.3)] | Grade 2 | - Withhold HERNEXEOS until resolution. - Resume HERNEXEOS at reduced dose level. - Permanently discontinue HERNEXEOS for recurrent ILD/pneumonitis.
Interstitial Lung Disease/Pneumonitis [see Warnings and Precautions (5.3)] | Grade 3 or Grade 4 | - Permanently discontinue HERNEXEOS.
Diarrhea [see Adverse Reactions (6.1)] | Grade 2 | - Maintain HERNEXEOS dose. - Initiate anti-diarrheal treatment.
Diarrhea [see Adverse Reactions (6.1)] | Grade 2 lasting ≥ 2 days despite anti-diarrheal treatment | - Interrupt HERNEXEOS until recovered to ≤ Grade 1. - Resume HERNEXEOS at reduced dose level.
Diarrhea [see Adverse Reactions (6.1)] | Grade 3 or Grade 4 | - Interrupt HERNEXEOS until recovered to ≤ Grade 1. - Resume HERNEXEOS at reduced dose level. - Permanently discontinue HERNEXEOS if diarrhea does not resolve to ≤ Grade 1 within 14 days, despite optimal supportive care (including anti-diarrheal treatment) and treatment interruption.
Other Adverse Reactions [see Adverse Reactions (6.1)] | Grade 3 | - Interrupt HERNEXEOS until recovered to ≤ Grade 1 or baseline. - Resume HERNEXEOS at reduced dose level.
Other Adverse Reactions [see Adverse Reactions (6.1)] | Grade 4 | - Permanently discontinue HERNEXEOS.
ALT = alanine aminotransferase; AST = aspartate aminotransferase; CTCAE = Common Terminology Criteria for Adverse Events; ULN = upper limit of normal

2.4 Dosage Modifications for Drug Interactions

Strong CYP3A Inducers

Avoid concomitant use of strong CYP3A inducers with HERNEXEOS.

If concomitant use cannot be avoided, increase the HERNEXEOS dose based on body weight [see Drug Interactions (7.1)]:

- < 90 kg: from 120 mg to 240 mg
- ≥ 90 kg: from 180 mg to 360 mg

After discontinuing a CYP3A inducer, resume the HERNEXEOS dose (7 to 14 days after discontinuing the CYP3A inducer) that was taken prior to initiating the CYP3A inducer.

3 DOSAGE FORMS AND STRENGTHS

60 mg tablets: yellow, oval, biconvex, film-coated tablets, debossed with "L6" on one side and the Boehringer Ingelheim company symbol on the other side. Each tablet contains 60 mg of zongertinib.

4 CONTRAINDICATIONS

None.

5 WARNINGS AND PRECAUTIONS

5.1 Hepatotoxicity

HERNEXEOS can cause severe and life-threatening hepatotoxicity, including drug induced liver injury. In a pooled safety population [see Adverse Reaction (6.1)], based on adverse reaction data, hepatotoxicity occurred in 27% of patients treated with HERNEXEOS. Grade 3 drug induced liver injury occurred in 1.5% and Grade 4 in 0.4% of patients treated with HERNEXEOS. Grade 3 hepatic failure occurred in 0.4% of patients treated with HERNEXEOS.

Based on laboratory data, 35% of patients treated with HERNEXEOS experienced increased alanine aminotransferase (ALT), including 4.3% Grade 3 and 1.2% Grade 4. Increased aspartate aminotransferase (AST) occurred in 31% of patients treated with HERNEXEOS, including 3.5% Grade 3 and 0.8% Grade 4. Increased bilirubin occurred in 20% of patients treated with HERNEXEOS, including 0.8% Grade 3 and 0.4% Grade 4.

HERNEXEOS was interrupted for an adverse reaction of hepatotoxicity in 8% of patients, the dose was reduced in 3.5% and permanently discontinued in 1.5%.

Monitor liver function tests including ALT, AST, and total bilirubin at baseline prior to administration of HERNEXEOS, every 2 weeks during the first 12 weeks, and then monthly thereafter as clinically indicated, with more frequent testing in patients who develop transaminase elevations. Interrupt, reduce the dose, or permanently discontinue HERNEXEOS based on the severity of the adverse reaction [see Dosage and Administration (2.3)].

5.2 Left Ventricular Dysfunction

HERNEXEOS can cause severe left ventricular dysfunction. Left ventricular ejection fractions (LVEF) decrease occurred with anti-HER2 therapies, including HERNEXEOS. Treatment with HERNEXEOS has not been studied in patients with a history of clinically significant cardiac disease or LVEF less than 50% prior to initiation of treatment.

In the pooled safety population [see Adverse Reactions (6.1)], LVEF decrease occurred in 6% of patients treated with HERNEXEOS, including 1.9% Grade 3. Two patients with Grade 3 LVEF decrease required permanent discontinuation. The median time to onset of decreased LVEF was 9 weeks (range: 2.9 to 63 weeks).

Before initiating HERNEXEOS, evaluate LVEF and monitor at regular intervals during treatment and as clinically indicated. Interrupt, reduce the dose, or permanently discontinue HERNEXEOS based on the severity of the adverse reaction [see Dosage and Administration (2.3)].

5.3 Interstitial Lung Disease/Pneumonitis

HERNEXEOS can cause severe and life-threatening interstitial lung disease (ILD)/pneumonitis.

In the pooled safety population [see Adverse Reactions (6.1)], ILD/pneumonitis occurred in 1.2% of patients (N=3) treated with HERNEXEOS. The median time to first onset of ILD/pneumonitis was 19 weeks (range: 6 to 65 weeks). One patient was able to resume therapy after resolution of pneumonitis. One patient required permanent discontinuation and one patient died with unresolved pneumonitis > 30 days after discontinuing HERNEXEOS.

Monitor patients for new or worsening symptoms indicative of ILD/pneumonitis (e.g., dyspnea, cough, fever). Interrupt, reduce the dose or permanently discontinue HERNEXEOS based on severity of confirmed ILD/pneumonitis [see Dosage and Administration (2.3)].

5.4 Embryo-Fetal Toxicity

Based on findings from animal studies and its mechanism of action, HERNEXEOS can cause fetal harm when administered to a pregnant woman. In an animal reproduction study, oral administration of zongertinib to pregnant rats during the period of organogenesis caused structural abnormalities and alterations to growth at maternal exposures ≥ 19 times the human exposure based on AUC at the recommended dose.

Advise pregnant women and females of reproductive potential of the potential risk to a fetus. Advise females of reproductive potential to use effective contraception during treatment with HERNEXEOS and for 2 weeks after the last dose [see Use in Specific Populations (8.1, 8.3)].

6 ADVERSE REACTIONS

The following adverse reactions are discussed in greater detail in other sections of the labeling:

- Hepatotoxicity [see Warnings and Precautions (5.1)]
- Left Ventricular Dysfunction [see Warnings and Precautions (5.2)]
- Interstitial Lung Disease/Pneumonitis [see Warnings and Precautions (5.3)]

6.1 Clinical Trials Experience

Because clinical trials are conducted under widely varying conditions, adverse reaction rates observed in the clinical trials of a drug cannot be directly compared to rates in the clinical trials of another drug and may not reflect the rates observed in clinical practice.

The pooled safety population described in WARNINGS AND PRECAUTIONS reflects exposure to HERNEXEOS in 260 patients with unresectable or metastatic non-squamous NSCLC with HER2 (ERBB2) mutations who received HERNEXEOS as a single agent at 120 mg orally once daily until disease progression or unacceptable toxicity in Beamion LUNG-1 [see Clinical Studies (14)]. Among 260 patients who received HERNEXEOS, 58% of patients were exposed for 6 months or longer and 13% were exposed for greater than one year. In this pooled safety population, the most common (> 20%) adverse reactions were diarrhea (53%), hepatotoxicity (27%), rash (27%), fatigue (22%), and nausea (21%). The most common (≥ 2%) Grade 3 or 4 laboratory abnormalities were decreased lymphocytes (9%), increased alanine aminotransferase (5%), increased aspartate aminotransferase (4.3%), decreased potassium (2.7%), and increased gamma glutamyl transferase (2.7%).

Beamion LUNG-1

The safety of HERNEXEOS was evaluated in Beamion LUNG-1 in 105 patients with previously treated unresectable or metastatic non-squamous NSCLC with HER2 tyrosine kinase domain (TKD) mutations; all patients had received prior platinum-based chemotherapy, and 34 patients had received prior treatment with a HER2-directed antibody drug conjugate (ADC) [see Clinical Studies (14)]. Patients received HERNEXEOS as a single agent at 120 mg once daily until disease progression or unacceptable toxicity. Among patients who received HERNEXEOS, 72% were exposed for 6 months or longer and 30% were exposed for greater than one year. The median age of patients who received HERNEXEOS was 61 years (range 30 to 85), 69% were female, 40% White, 49% Asian, and 0% Black or African American; 11% had unknown race data; 1.9% were of Hispanic or Latino ethnicity; and 33% had an Eastern Cooperative Oncology Group (ECOG) performance score of 0 and 67% had an ECOG performance score of 1.

Serious adverse reactions occurred in 34% of patients receiving HERNEXEOS. Serious adverse reactions in ≥ 2% of patients included dyspnea (4.8%), pulmonary embolism (4.8%), hepatotoxicity (2.9%), and pneumonia (2.9%). Fatal adverse reactions occurred in 1% of patients who received HERNEXEOS, due to pneumonia.

Permanent discontinuation of HERNEXEOS due to an adverse reaction occurred in 2.9% of patients. Adverse reactions which resulted in permanent discontinuation of HERNEXEOS were hepatotoxicity, increased blood alkaline phosphatase, dyspnea, increased gamma-glutamyl transferase, hemoptysis, and pyrexia.

Dosage interruption of HERNEXEOS due to an adverse reaction occurred in 28% of patients. Adverse reactions which required dosage interruption in ≥ 2% of patients were hepatotoxicity, decreased ejection fraction, and rash.

Dose reductions of HERNEXEOS due to adverse reactions occurred in 7% of patients. Adverse reactions which required dose reductions in ≥ 1% of patients were hepatotoxicity, decreased ejection fraction, increased blood creatinine phosphokinase, increased gamma-glutamyl transferase, and decreased neutrophil count.

Tables 3 and 4 summarize adverse reactions and laboratory abnormalities observed in Beamion LUNG-1.

Table 3 Adverse Reactions (≥ 15%) in Patients with Non-Squamous NSCLC with HER2 TKD Mutations Who Received HERNEXEOS in Beamion LUNG-1
Adverse Reaction | HERNEXEOS N = 105
Adverse Reaction | All Grades^1 % | Grade 3 or 4 %
Gastrointestinal Disorders
Diarrhea* | 52 | 1
Nausea | 24 | 1
Vomiting | 15 | 1.9
Skin and Subcutaneous Tissue Disorders
Rash* | 32 | 1
Nail disorders* | 19 | 0
General Disorders
Fatigue* | 25 | 0
Respiratory, Thoracic and Mediastinal Disorders
Cough* | 24 | 0
Dyspnea* | 15 | 6
Musculoskeletal and Connective Tissue Disorders
Musculoskeletal pain* | 24 | 1.9
Infections and Infestations
Upper respiratory tract infections* | 21 | 0
Events were graded using NCI CTCAE version 5.0.
^1No Grade 4 or Grade 5 adverse reactions occurred.
*Grouped term.

Clinically relevant adverse reactions in < 15% of patients who received HERNEXEOS included stomatitis, dry skin, pruritus, and peripheral neuropathy.

Table 4 Select Laboratory Abnormalities (≥ 20%) in Patients with Non-Squamous NSCLC with HER2 TKD Mutations Who Received HERNEXEOS in Beamion LUNG-1
Laboratory Parameter | HERNEXEOS N = 105
Laboratory Parameter | All Grades^1 % | Grade 3 or 4 %
Hematology
Lymphocytes decreased | 52 | 15
Leukocytes decreased | 43 | 1
Hemoglobin decreased | 37 | 0
Activated partial thromboplastin time increased | 25 | 0
Platelets decreased | 23 | 1
Chemistry
Alanine aminotransferase increased | 39 | 7
Aspartate aminotransferase increased | 33 | 2.9
Lipase increased | 30 | 0
Bilirubin increased | 26 | 1
Triglycerides increased | 26 | 0
Calcium decreased | 25 | 0
Amylase increased | 24 | 0
Sodium decreased | 23 | 0
Creatinine kinase increased | 22 | 0
Albumin decreased | 21 | 0
Cholesterol increased | 20 | 1.4
Alkaline phosphatase increased | 20 | 1
Magnesium decreased | 20 | 1
Potassium decreased | 20 | 0
Events were graded using NCI CTCAE version 5.0.
^1No Grade 5 adverse reactions occurred.

7 DRUG INTERACTIONS

7.1 Effects of Other Drugs on HERNEXEOS

Avoid concomitant use of HERNEXEOS with strong CYP3A inducers. If concomitant use cannot be avoided, increase HERNEXEOS dose as recommended [see Dosage and Administration (2.4)].

Zongertinib is a CYP3A substrate. Strong CYP3A4 inducers decrease zongertinib exposure [see Clinical Pharmacology (12.3)], which may reduce effectiveness of HERNEXEOS.

7.2 Effects of HERNEXEOS on Other Drugs

BCRP Substrates

Avoid concomitant use of HERNEXEOS with certain BCRP substrates where minimal concentration changes may lead to serious adverse reactions. If coadministration cannot be avoided, monitor for increased adverse reactions and follow recommendations provided in the approved product labeling for the BCRP substrate. For other BCRP substrates, monitor for increased adverse reactions and adjust the dosages of those substrates as clinically appropriate.

Zongertinib is a BCRP inhibitor. HERNEXEOS increases exposure of BCRP substrates [see Clinical Pharmacology (12.3)], which may increase the risk of adverse reactions related to these substrates.

8 USE IN SPECIFIC POPULATIONS

8.1 Pregnancy

Risk Summary

Based on findings from animal studies and its mechanism of action [see Clinical Pharmacology (12.1)], HERNEXEOS can cause fetal harm when administered to a pregnant woman. There are no available data on the use of HERNEXEOS in pregnant women to inform a drug-associated risk. Oral administration of zongertinib to pregnant rats during the period of organogenesis caused structural abnormalities and alterations to growth at maternal exposures ≥ 19 times the human exposure based on AUC at the recommended dose [see Data]. Advise pregnant women and females of reproductive potential of the potential risk to a fetus.

In the U.S. general population, the estimated background risk of major birth defects and miscarriage in clinically recognized pregnancies is 2% to 4% and 15% to 20%, respectively.

Data

Animal Data

In an embryo-fetal development study, pregnant rats received oral doses of 10, 30, or 60 mg/kg/day of zongertinib during the period of organogenesis (gestation day 7 to 18). Zongertinib caused decreased fetal weights, delayed development of the urinary system, and kidney hydronephrosis at 60 mg/kg/day (approximately 19 times the human exposure based on AUC at the recommended dose). In an embryo-fetal development study in rabbits, there were no adverse embryo-fetal findings in pregnant animals administered oral doses of zongertinib up to 120 mg/kg/day (2.4 times the human exposure based on AUC at the recommended dose) during the period of organogenesis (gestation day 6 to 19).

A literature-based assessment of the effects on reproduction demonstrated that mice expressing catalytically inactive HER2 die at mid-gestation due to cardiac dysfunction.

8.2 Lactation

Risk Summary

There are no data on the presence of zongertinib or its metabolites in human milk, the effects on the breastfed child, or the effects on milk production. Because of the potential for serious adverse reactions in breastfed children, advise women not to breastfeed during treatment with HERNEXEOS and for 2 weeks after the last dose.

8.3 Females and Males of Reproductive Potential

Based on findings from animal studies and its mechanism of action, HERNEXEOS can cause embryo-fetal harm when administered to a pregnant woman [see Use in Specific Populations (8.1)].

Pregnancy Testing

Verify the pregnancy status of females of reproductive potential prior to initiating HERNEXEOS.

Contraception

Females

Advise females of reproductive potential to use effective contraception during treatment with HERNEXEOS and for 2 weeks after the last dose.

Infertility

Females

Based on findings from animal studies, HERNEXEOS may impair fertility in females. The effects in female animals were reversible [see Nonclinical Toxicology 13.1].

Males

Based on findings from animal studies, HERNEXEOS may impair fertility in males of reproductive potential. The effect on testes in animals was not reversible within a 4-week recovery period [see Nonclinical Toxicology 13.1].

8.4 Pediatric Use

The safety and effectiveness of HERNEXEOS have not been established in pediatric patients.

8.5 Geriatric Use

Of the 260 patients with non-squamous NSCLC with HER2 (ERBB2) mutations who received HERNEXEOS in clinical studies, 46% were 65 years of age and older and 12% were 75 years and older. No overall differences in safety or effectiveness of HERNEXEOS were observed between older and younger adult patients.

10 OVERDOSAGE

Overdose in one patient who ingested 600 mg of HERNEXEOS resulting in nausea and vomiting.

11 DESCRIPTION

HERNEXEOS tablets for oral administration contain zongertinib, a kinase inhibitor. The chemical name of zongertinib is 2-Propenamide, N-[1-[8-[[3-methyl-4-[(1-methyl-1H-benzimidazol-5-yl)oxy]phenyl] amino]pyrimido[5,4-d]pyrimidin-2-yl]-4-piperidinyl]-. Its molecular formula is C29H29N9O2 and the molecular weight is 535.6. The structural formula is:

Zongertinib is a yellow to dark yellow or orange solid. Zongertinib is slightly soluble at pH 1.2, and practically insoluble at pHs 3.6, 4.5, 5.4 and 6.8.

Each film-coated tablet of HERNEXEOS contains 60 mg of zongertinib and the following inactive ingredients: colloidal silicon dioxide, croscarmellose sodium, hypromellose acetate succinate, mannitol, microcrystalline cellulose, and sodium stearyl fumarate. In addition, the film-coating contains the following inactive ingredients: ferric oxide (yellow), glycerol mono and dicaprylocaprate, polyvinyl alcohol, sodium lauryl sulfate, talc, and titanium dioxide.

12 CLINICAL PHARMACOLOGY

12.1 Mechanism of Action

Zongertinib is a kinase inhibitor of human epidermal growth factor receptor 2 (HER2). In vitro, zongertinib inhibited phosphorylation of HER2, downstream signaling of HER2 (phosphorylation of ERK), and proliferation of lung cancer cells harboring HER2 tyrosine kinase domain activating mutations. In vivo, zongertinib demonstrated anti-tumor activity in mouse xenograft models of NSCLC harboring HER2 tyrosine kinase domain activating mutations.

12.2 Pharmacodynamics

The exposure-response relationship and time-course of pharmacodynamic response of zongertinib have not been fully characterized.

Cardiac Electrophysiology

At 2.6 times the mean maximal concentration provided by the recommended dose of 120 mg, a mean increase in the QTc interval > 20 ms was not observed.

12.3 Pharmacokinetics

Zongertinib pharmacokinetics were observed at steady state in patients with advanced or metastatic solid tumors with HER2 aberrations at the approved recommended dosage and are presented as geometric mean (CV%), unless otherwise specified.

Zongertinib maximum concentration (Cmax,ss) is 3.0 (37%) µmol/L and the total systemic exposure (AUC) is 34 (34%) µmol*h/L following HERNEXEOS 120 mg orally daily. Zongertinib Cmax and AUC increase in an approximately dose proportional manner across the dose range of 60 mg (0.5 times the approved recommended dosage) to 360 mg (3 times the approved recommended dosage). Zongertinib accumulation is approximately 1.5-fold for AUC and 1.3-fold for Cmax at the approved recommended dosage. Steady state is achieved within 2.5 days.

Absorption

Zongertinib median (min, max) time to maximum plasma concentration (Tmax) is approximately 2 hours (min, max: 2, 6 hours). Zongertinib absolute oral bioavailability is 76%.

Effect of Food

No clinically significant differences in zongertinib Cmax and AUC were observed following administration of a single 240 mg dose (2 times the approved recommended dose) with a high-fat meal (approximately 1,000 calories, approximately 50% fat).

Distribution

Zongertinib plasma protein binding is > 99%. The apparent (oral) volume of distribution is 118 L (29%).

Elimination

Zongertinib effective half-life is 12 hours (21%) with an apparent (oral) clearance of 115 mL/min (31%).

Metabolism

Based on in vitro metabolite profiling, CYP-mediated oxidation pathways represent 48% to 62% (mainly CYP3A4 and CYP3A5), glucuronidation 13% to 25% (mainly UGT1A4), and glutathione conjugation 13% to 26% of total hepatic metabolism. Unchanged zongertinib represented the majority (75%) of total radioactivity in plasma.

Excretion

After a single oral dose of radiolabeled zongertinib 60 mg to healthy participants, approximately 93% of the dose was recovered in feces (31% unchanged) and 1.3% in urine (0.2% unchanged).

Specific Populations

The apparent volume of distribution and clearance of zongertinib increase with increasing body weight (34 to 122 kg).

No clinically significant differences in the pharmacokinetics of zongertinib were observed based on age (30 to 88 years), sex, race (36% White, 49% Asian, 1.3% Black/African American), mild renal impairment (eGFR 60 to < 90 mL/min) or mild hepatic impairment (AST > ULN and total bilirubin ≤ ULN; or total bilirubin >1 to 1.5× ULN and any AST). The effect of moderate renal impairment (eGFR 30 to < 60 mL/min), severe renal impairment (eGFR 15 to < 30 mL/min), end-stage renal disease (eGFR < 15 mL/min), moderate hepatic impairment (total bilirubin > 1.5 to 3× ULN and any AST) or severe hepatic impairment (total bilirubin > 3× ULN and any AST) on the pharmacokinetics of zongertinib have not been studied.

Drug Interaction Studies

CYP3A Inducers: Zongertinib AUC decreased by 63% and Cmax decreased by 43% following concomitant use of carbamazepine (strong CYP3A inducer) 600 mg once daily for 7 days. The effect of concomitant use of moderate CYP3A inducers on zongertinib Cmax and AUC are unknown.

BCRP Substrates: Rosuvastatin (BCRP substrate) Cmax increased by 3-fold and AUC by 2.3-fold following concomitant use of a single dose of HERNEXEOS 120 mg daily for 12 days.

Other Drugs: No clinically significant differences in zongertinib pharmacokinetics were observed when used concomitantly with strong CYP3A, P-gp, BCRP inhibitors and rabeprazole (proton pump inhibitor). No clinically significant differences in the pharmacokinetics of the following were observed when used concomitantly with HERNEXEOS: midazolam (a CYP3A substrate), dabigatran (a P-gp substrate), metformin (a OCT2 and MATE1/2-K substrate), or repaglinide (a sensitive CYP2C8 substrate).

13 NONCLINICAL TOXICOLOGY

13.1 Carcinogenesis, Mutagenesis, Impairment of Fertility

Carcinogenesis

Carcinogenicity studies have not been conducted with zongertinib.

Mutagenesis

Zongertinib was not mutagenic in an in vitro bacterial reverse mutation (Ames) assay. Zongertinib was not genotoxic in an in vivo rat bone marrow micronucleus test and did not induce DNA breaks in a comet assay in liver or duodenum.

Impairment of Fertility

Dedicated animal fertility studies have not been conducted with zongertinib. In a 13-week repeat-dose toxicity study in rats, oral administration of zongertinib induced dose-dependent vacuolation in the testis at doses ≥ 10 mg/kg/day (≥ 5.7 times the human exposure based on AUC at the recommended dose), atrophy in the prostate gland at doses ≥ 30 mg/kg/day (≥ 8.4 times the human exposure based on AUC at the recommended dose), and atrophy in the uterus and hyperplasia/hyperkeratosis of the cervix and vagina at a dose of 90 mg/kg/day (approximately 17 times the human exposure based on AUC at the recommended dose). Findings in reproductive organs in female rats and prostate gland atrophy in male rats were reversible following a 4-week recovery period. Vacuolation in the testis of male rats was not reversible within a 4-week recovery period.

13.2 Animal Toxicology and/or Pharmacology

In a 4-week repeat-dose toxicology study in dogs, oral administration of zongertinib induced lesions of the oral mucosa (hard palate, buccal mucosa, tongue, lips) at doses ≥ 10 mg/kg/day (≥ 0.3 times the human exposure based on AUC at the recommended dose), which correlated with histologic erosion/ulcer and impaired food consumption. These findings were not present following a 4-week recovery period.

14 CLINICAL STUDIES

HERNEXEOS was evaluated in Beamion LUNG-1 (NCT04886804), a single arm, open-label, multi-center, multi-cohort trial. Eligible patients were required to have unresectable or metastatic NSCLC with HER2 (ERBB2) mutations. Patients with stable brain metastases were eligible to enroll. The study excluded patients who had a history of non-infectious interstitial lung disease/pneumonitis.

Patients received HERNEXEOS 120 mg orally once daily until disease progression or unacceptable toxicity. The major efficacy outcome measures were objective response rate (ORR) and duration of response (DOR) by Response Evaluation Criteria in Solid Tumors (RECIST) version 1.1 as assessed by blinded independent central review (BICR).

The efficacy population included 71 patients with unresectable or metastatic, non-squamous NSCLC with HER2 (ERBB2) tyrosine kinase domain (TKD) mutations based on prospective local testing. Of those, tumor tissue samples from 52% (37/71) of patients were retrospectively tested using Oncomine™ Dx Target Test (Life Technologies Corporation, Tissue-test). While 84% (31/37) of samples were positive for HER2 (ERBB2) TKD mutations, 2.7% (1/37) did not have HER2 (ERBB2) TKD mutations identified, and 13.5% (5/37) were unevaluable.

The baseline demographic and disease characteristics of the efficacy population were: 62 years (range: 30 to 80); 70% female, 55% Asian, 35% White, 0% Black or African American; 10% had unknown race data; 1.4% were of Hispanic or Latino ethnicity; 39% Eastern Cooperative Oncology Group (ECOG) performance status (PS) 0 and 61% ECOG PS 1; 65% never smoked; 100% metastatic disease; and 37% with brain metastases. The median number of prior therapies was 1 (range: 1 to 10); 100% of patients had prior platinum therapy and 78% had prior treatment with anti-PD-1/PD-L1 antibody. No patient had received previous treatment with a HER2-targeted tyrosine kinase inhibitor (TKI) or HER2-targeted antibody-drug conjugate (ADC).

Efficacy results are summarized in Table 5.

Table 5 Efficacy Results for Beamion LUNG-1
Efficacy Parameter | HERNEXEOS N = 71
Objective Response Rate (ORR), % (95% CI)^1 | 75 (63, 83)
Complete response, % | 6
Partial response, % | 69
Duration of Response (DOR) | N = 53
Range, months | 1.3+, 15+
DOR ≥ 6 months,^2 % | 58
Abbreviation: CI = Confidence Interval, +: Ongoing response.
^1Based on Wilson confidence interval.
^2Based on observed duration of response.

Among the 71 patients, 5 patients had measurable CNS metastases at baseline as assessed by BICR and had not received radiation therapy to the brain within 2 months prior to treatment with HERNEXEOS. Based on Response Assessment in Neuro-Oncology Brain Metastases (RANO-BM) criteria per BICR, responses were observed in 3 patients.

HERNEXEOS was also evaluated in 34 patients with unresectable or metastatic HER2 (ERBB2) TKD mutation-positive non-squamous NSCLC who had received previous treatment with platinum-based chemotherapy and a HER2-targeted ADC. Eligibility criteria were otherwise similar to the efficacy population described above. The median age was 58 years (range: 31 to 85); 65% female, 35% Asian, 50% White, 0% Black or African American; 15% had unknown race data; and 2.9% were of Hispanic or Latino ethnicity. Baseline ECOG performance status was 0 (21%) or 1 (79%); 65% never smoked. 100% patients had metastatic disease and 74% had brain metastases. The median number of prior therapies was 3 (range: 1 to 8); 100% of patients had prior platinum therapy and 77% had prior treatment with anti-PD-1/PD-L1 antibody; 2.9% of patients had received previous treatment with a HER2-targeted TKI. Confirmed ORR by RECIST v1.1 based on BICR was 44% (95% CI 29, 61), with 2.9% of patients having a complete response. Median DOR was 5.4 months (95% CI 2.8, not estimable), and 27% of responders had an observed DOR ≥ 6 months.

16 HOW SUPPLIED/STORAGE AND HANDLING

60 mg tablets: yellow, oval, biconvex, film-coated, debossed with "L6" on one side and the Boehringer Ingelheim company symbol on the other side. They are packaged in a bottle containing two silica gel desiccants and with a child-resistant closure, available as follows:

Cartons containing one bottle of 60 tablets each | NDC: 0597-9257-86
Cartons containing one bottle of 30 tablets each | NDC: 0597-9257-59

Storage and Handling

Store at 20°C to 25°C (68°F to 77°F), excursions permitted to 15°C to 30°C (59°F to 86°F) [see USP Controlled Room Temperature].

Store in the original container to protect from moisture. Keep the bottle tightly closed. Do not remove the desiccants. Once opened, use within 3 months. Discard any unused tablets 3 months after opening the bottle.

17 PATIENT COUNSELING INFORMATION

Advise the patient to read the FDA-approved patient labeling (Patient Information).

Hepatotoxicity

Inform patients that HERNEXEOS can cause severe and life-threatening hepatotoxicity and that they will need to undergo lab tests to monitor liver enzymes during treatment [see Warnings and Precautions (5.1)]. Advise patients to immediately contact their healthcare provider for signs and symptoms of hepatotoxicity.

Left Ventricular Dysfunction

Inform patients that HERNEXEOS can cause severe left ventricular dysfunction. Advise patients to immediately contact their healthcare provider for new or worsening cardiovascular symptoms [see Warnings and Precautions (5.2)].

Interstitial Lung Disease (ILD)/Pneumonitis

Inform patients that HERNEXEOS can cause severe or life-threatening ILD/pneumonitis. Advise patients to immediately contact their healthcare provider for new or worsening respiratory symptoms [see Warnings and Precautions (5.3)].

Diarrhea

Inform patients that HERNEXEOS can cause diarrhea. Advise patients to immediately contact their healthcare provider for signs and symptoms of diarrhea [see Adverse Reactions (6.1)].

Embryo-Fetal Toxicity

Advise females of reproductive potential of the potential risk to a fetus. Advise females to inform their healthcare provider of a known or suspected pregnancy. Advise females of reproductive potential to use effective contraception during treatment with HERNEXEOS and for 2 weeks after the last dose [see Warnings and Precautions (5.4) and Use in Specific Populations (8.1, 8.3)].

Lactation

Advise women not to breastfeed during treatment with HERNEXEOS and for 2 weeks after the last dose [see Use in Specific Populations (8.2)].

Infertility

Advise females and males of reproductive potential that HERNEXEOS may impair fertility [see Use in Specific Populations (8.3)].

Administration Instructions

Instruct patients weighing < 90 kg to take two 60 mg tablets once daily to achieve a complete 120 mg dose and instruct patients weighing ≥ 90 kg to take three 60 mg tablets once daily to achieve a complete 180 mg dose [see Dosage and Administration (2.2)]. HERNEXEOS film-coated tablets can be taken with or without food [see Clinical Pharmacology (12.3)]. Instruct patients to swallow HERNEXEOS tablets whole with water. Do not split, crush, or chew tablets.

Inform patients that if they miss a dose of HERNEXEOS within 12 hours, they should take it as soon as they remember. If the next dose is missed by more than 12 hours, the patient should skip the missed dose and wait until the next scheduled dose [see Dosage and Administration (2.2)].

If a dose is vomited, do not take an additional dose. Take the next dose at the regularly scheduled time.

Distributed by:
Boehringer Ingelheim Pharmaceuticals, Inc.
Ridgefield, CT 06877 USA

Licensed from:
Boehringer Ingelheim International GmbH, Ingelheim, Germany

HERNEXEOS is a registered trademark of and used under license from Boehringer Ingelheim International GmbH.

The other brands listed are trademarks of their owners and are not trademarks of Boehringer Ingelheim Pharmaceuticals, Inc.

Copyright 2026 Boehringer Ingelheim International GmbH
ALL RIGHTS RESERVED

COL13134DK062025
SPL13174B

Patient Information
HERNEXEOS® (her-nex-ee-ose)
(zongertinib tablets)

What is HERNEXEOS?
HERNEXEOS is a prescription medicine used to treat adults with a type of lung cancer called non-squamous non-small cell lung cancer (NSCLC) that:

- cannot be removed by surgery or that has spread to other parts of your body (metastatic), and
- has a certain mutation in the human epidermal growth factor receptor 2 (HER2) gene, and
- who have previously received treatment by mouth or injection (systemic therapy).

Your healthcare provider will perform a test to make sure HERNEXEOS is right for you.
It is not known if HERNEXEOS is safe and effective in children.

Before taking HERNEXEOS, tell your healthcare provider about all of your medical conditions, including if you:

- have liver problems
- have heart problems
- have lung or breathing problems other than lung cancer
- are pregnant or plan to become pregnant. HERNEXEOS can harm your unborn baby.
  Females who are able to become pregnant:
  - Your healthcare provider will do a pregnancy test before you start treatment with HERNEXEOS.
  - Use an effective form of birth control (contraception) during treatment with HERNEXEOS and for 2 weeks after your last dose.
  - Talk to your healthcare provider about birth control methods that might be right for you during this time.
  - Tell your healthcare provider right away if you become pregnant or think you are pregnant during treatment with HERNEXEOS.
- are breastfeeding or plan to breastfeed. It is not known if HERNEXEOS passes into your breastmilk. Do not breastfeed during treatment and for 2 weeks after your last dose of HERNEXEOS.

Tell your healthcare provider about all the medicines you take, including prescription and over-the-counter medicines, vitamins, and herbal supplements. HERNEXEOS may affect the way other medicines work, and other medicines may affect how HERNEXEOS works.
Know the medicines you take. Keep a list of them to show your healthcare provider or pharmacist when you get a new medicine.

How should I take HERNEXEOS?

- Take HERNEXEOS exactly as your healthcare provider tells you to take it.
- Your healthcare provider may change your dose if needed. Do not change your dose or stop taking HERNEXEOS unless your healthcare provider tells you to.
- Take HERNEXEOS 1 time a day, with or without food.
- Swallow HERNEXEOS tablets whole with water. Do not split, crush, or chew tablets.
- If you miss a dose of HERNEXEOS, take it as soon as you remember within 12 hours. If you missed your dose by more than 12 hours, skip the missed dose and take your next dose at your next scheduled time.
- If you vomit after taking a dose of HERNEXEOS, do not take an extra dose. Take your next dose at your regularly scheduled time.
- If you take too much HERNEXEOS, call your healthcare provider or go to the nearest hospital emergency room right away.

What are the possible side effects of HERNEXEOS?
HERNEXEOS may cause serious side effects, including:

- liver problems. Liver problems are common with HERNEXEOS and can be severe and life-threatening. Your healthcare provider will do blood tests to check your liver function before you start taking HERNEXEOS and during your treatment. Tell your healthcare provider right away if you develop any signs and symptoms of liver problems, including:

- yellowing of your skin or the white part of your eyes (jaundice)
- dark or brown (tea colored) urine
- pain on the upper right side of your stomach area (abdomen)

- bleeding or bruising more easily than normal
- feeling very tired
- loss of appetite
- nausea or vomiting

- heart problems that may affect your heart's ability to pump blood. HERNEXEOS can cause heart problems. Your healthcare provider will do tests to check your heart function before you start taking HERNEXEOS and during treatment. Tell your healthcare provider right away if you have any new or worsening symptoms of heart problems, including:

- feeling like your heart is pounding or racing
- dizziness
- tiredness
- feeling lightheaded

- shortness of breath
- loss of consciousness
- coughing
- swelling of your legs, ankles or feet

- lung problems. HERNEXEOS can cause lung problems that are severe or life-threatening. Tell your healthcare provider right away if you have any new or worsening symptoms of lung problems, including trouble breathing, shortness of breath, cough, or fever.

Your healthcare provider may temporarily stop, decrease your dose, or permanently stop treatment with HERNEXEOS if you have serious side effects.

The most common side effects of HERNEXEOS include:

- diarrhea. HERNEXEOS can cause severe diarrhea. Tell your healthcare provider right away if you have diarrhea.
- liver problems
- rash
- feeling tired
- nausea

The most common severe abnormal blood tests include decreased white blood cell count, increased liver function tests and decreased potassium levels.
HERNEXEOS may cause fertility problems in females and males, which may affect your ability to have children. Talk to your healthcare provider if this is a concern for you.
These are not all of the possible side effects of HERNEXEOS.
Call your doctor for medical advice about side effects. You may report side effects to FDA at 1-800-FDA-1088.

How should I store HERNEXEOS?

- Store HERNEXEOS at room temperature between 68°F to 77°F (20°C to 25°C).
- Store HERNEXEOS tablets in the original bottle.
- Keep the HERNEXEOS bottle tightly closed.
- The HERNEXEOS bottle contains two desiccants to help keep your tablets dry (protect from moisture). Do not remove the desiccants from the container after opening. Do not eat or swallow the desiccants.
- HERNEXEOS comes in a child-resistant bottle.
- HERNEXEOS must be used within 3 months of first opening the bottle. Throw away (discard) any unused tablets 3 months after opening the bottle.

Keep HERNEXEOS and all medicines out of the reach of children.

General information about the safe and effective use of HERNEXEOS.
Medicines are sometimes prescribed for purposes other than those listed in a Patient Information leaflet. Do not use HERNEXEOS for any condition for which it was not prescribed. Do not give HERNEXEOS to other people, even if they have the same symptoms you have. It may harm them. You can ask your pharmacist or healthcare provider for information about HERNEXEOS that is written for health professionals.

What are the ingredients in HERNEXEOS?
Active ingredient: zongertinib
Inactive ingredients: colloidal silicon dioxide, croscarmellose sodium, hypromellose acetate succinate, mannitol, microcrystalline cellulose, and sodium stearyl fumarate. The film-coating contains ferric oxide (yellow), glycerol mono and dicaprylocaprate, polyvinyl alcohol, sodium lauryl sulfate, talc, and titanium dioxide.

Distributed by: Boehringer Ingelheim Pharmaceuticals, Inc., Ridgefield, CT 06877 USA
Licensed from: Boehringer Ingelheim International GmbH, Ingelheim, Germany
HERNEXEOS is a registered trademark of and used under license from Boehringer Ingelheim International GmbH.
Copyright © 2025 Boehringer Ingelheim International GmbH ALL RIGHTS RESERVED
COL13134AH062025
For more information about HERNEXEOS, including the current prescribing information and Patient Information, go to www.hernexeos.com, scan the code, or call Boehringer Ingelheim Pharmaceuticals, Inc. at 1-800-542-6257.

This Patient Information has been approved by the U.S. Food and Drug Administration.

Issued: Aug 2025

PRINCIPAL DISPLAY PANEL - 60 mg Tablet Bottle Carton - NDC 0597-9257-86

NDC 0597-9257-86

HERNEXEOS®
(zongertinib tablets)

60 mg

Pharmacist: Store and dispense in the
original container to protect from moisture.

60 tablets

Rx only

Boehringer
Ingelheim

PRINCIPAL DISPLAY PANEL - 60 mg Tablet Bottle Carton - NDC 0597-9257-59

NDC 0597-9257-59

HERNEXEOS®
(zongertinib tablets)

60 mg

Pharmacist: Store and dispense in the
original container to protect from moisture.

30 tablets

Rx only

Boehringer
Ingelheim